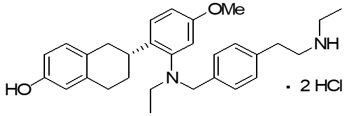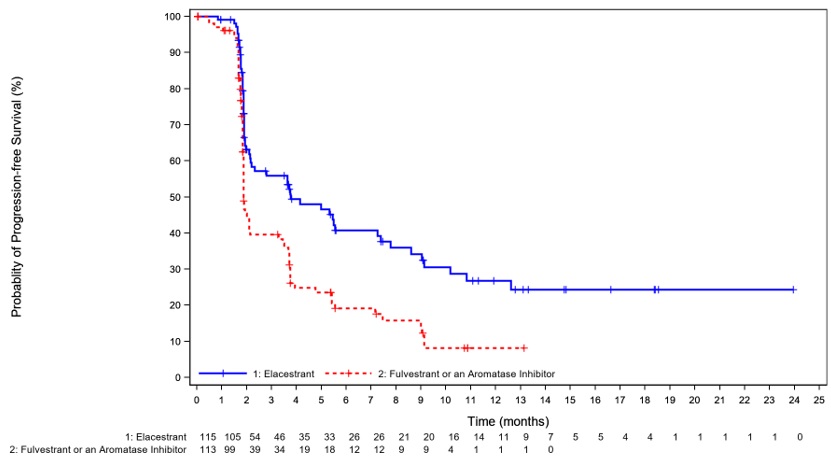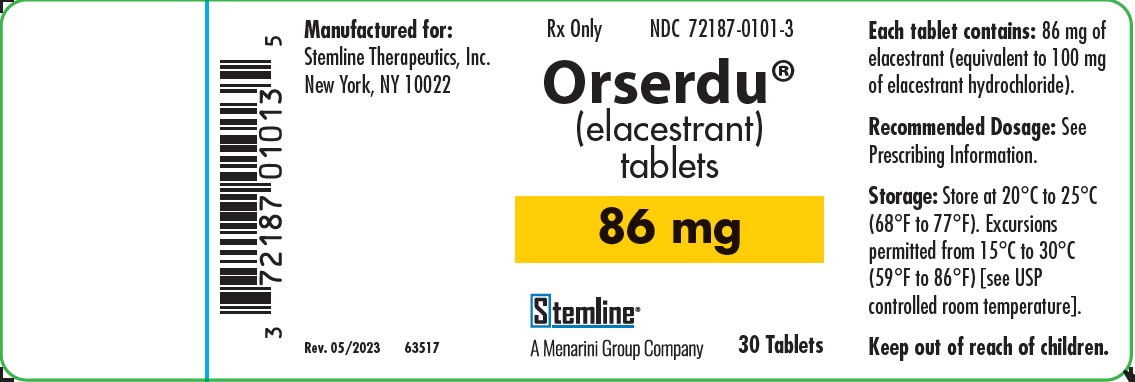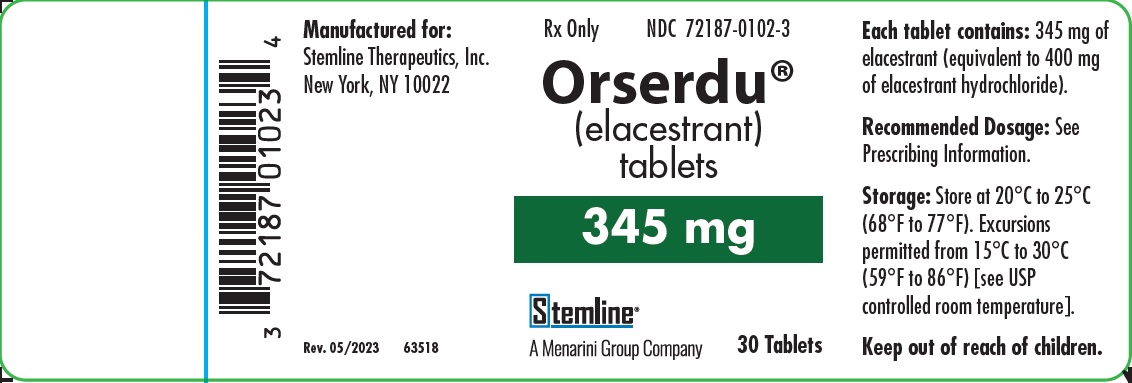 DRUG LABEL: ORSERDU
NDC: 72187-0101 | Form: TABLET, FILM COATED
Manufacturer: Stemline Therapeutics, Inc.
Category: prescription | Type: HUMAN PRESCRIPTION DRUG LABEL
Date: 20240802

ACTIVE INGREDIENTS: ELACESTRANT 86 mg/1 1

HIGHLIGHTS OF PRESCRIBING INFORMATION

These highlights do not include all the information needed to use ORSERDU safely and effectively. See full prescribing information for ORSERDU.
ORSERDU™ (elacestrant) tablets, for oral use
Initial U.S. Approval: 2023

1 INDICATIONS AND USAGE

ORSERDU is an estrogen receptor antagonist indicated for:

- treatment of postmenopausal women or adult men, with ER-positive, HER2-negative, ESR1-mutated advanced or metastatic breast cancer with disease progression following at least one line of endocrine therapy (1)

2 DOSAGE AND ADMINISTRATION

- Select patients for treatment with ORSERDU based on the presence of ESR1 mutations. (2.1)
- The recommended dosage of ORSERDU is one 345 mg tablet taken orally, once daily, with food (2.2)
- Dose interruption, reduction, or permanent discontinuation may be required due to adverse reactions. (2.3)

3 DOSAGE FORMS AND STRENGTHS

- Tablets: 345 mg and 86 mg (3)

4 CONTRAINDICATIONS

- None (4)

5 WARNINGS AND PRECAUTIONS

- Dyslipidemia: ORSERDU may cause hypercholesterolemia and hypertriglyceridemia. Monitor lipid profile prior to starting treatment and periodically thereafter. (5.1)
- Embryo-Fetal Toxicity: ORSERDU can cause fetal harm. Advise of the potential risk to a fetus and to use effective contraception. (5.2, 8.1, 8.3)

6 ADVERSE REACTIONS

The most common (>10%) adverse reactions, including laboratory abnormalities, of ORSERDU were musculoskeletal pain, nausea, increased cholesterol, increased AST, increased triglycerides, fatigue, decreased hemoglobin, vomiting, increased ALT, decreased sodium, increased creatinine, decreased appetite, diarrhea, headache, constipation, abdominal pain, hot flush, and dyspepsia. (6.1)

To report SUSPECTED ADVERSE REACTIONS, contact Stemline Therapeutics, Inc. at 1-877-332-7961 or FDA at 1-800-FDA-1088 or www.fda.gov/medwatch.

7 DRUG INTERACTIONS

- Strong and Moderate CYP3A4 Inducers: Avoid concomitant use with ORSERDU (7.1)
- Strong and Moderate CYP3A4 Inhibitors: Avoid concomitant use with ORSERDU (7.1)

8 USE IN SPECIFIC POPULATIONS

- Lactation: Advise not to breastfeed. (8.2)
- Hepatic impairment: Avoid use in patients with severe hepatic impairment (Child-Pugh C). Reduce the dosage for patients with moderate hepatic impairment (Child-Pugh B). (2.5, 8.6)

FULL PRESCRIBING INFORMATION

1 INDICATIONS AND USAGE

ORSERDU is indicated for the treatment of postmenopausal women or adult men with estrogen receptor (ER)-positive, human epidermal growth factor receptor 2 (HER2)‑negative, ESR1-mutated advanced or metastatic breast cancer with disease progression following at least one line of endocrine therapy.

2 DOSAGE AND ADMINISTRATION

2.1 Patient Selection

Select patients for treatment of ER-positive, HER2-negative advanced or metastatic breast cancer with ORSERDU based on the presence of ESR1 mutation(s) in plasma specimen using an FDA-approved test [see Indications and Usage (1) and Clinical Studies (14)].

Information on FDA-approved tests for detection of ESR1 mutations in breast cancer is available at: http://www.fda.gov/CompanionDiagnostics.

2.2 Recommended Dosage

The recommended dosage of ORSERDU is 345 mg taken orally with food once daily until disease progression or unacceptable toxicity occurs.

Take ORSERDU at approximately the same time each day. Take with food to reduce nausea and vomiting [see Adverse Reactions (6.1)].

Swallow ORSERDU tablet(s) whole. Do not chew, crush, or split prior to swallowing. Do not take any ORSERDU tablets that are broken, cracked, or that look damaged.

If a dose is missed for more than 6 hours or vomiting occurs, skip the dose and take the next dose the following day at its regularly scheduled time.

2.3 Dosage Modifications for Adverse Reactions

The recommended dose reduction levels for adverse reactions are listed in Table 1:

Table 1: ORSERDU Dose Reduction Levels for Adverse Reactions

Dose Reduction | Dosage | Number and Strength of Tablets
First-dose reduction | 258 mg once daily | Three 86 mg tablets
Second-dose reduction | 172 mg once daily^1 | Two 86 mg tablets
^1 If further dose reduction below 172 mg once daily is required, permanently discontinue ORSERDU.

Recommended dosage modifications of ORSERDU for adverse reactions are provided in Table 2 [see Adverse Reactions (6.1)].

Table 2: ORSERDU Dosage Modification Guidelines for Adverse Reactions

Severity | Dosage Modification
Grade 1 | Continue ORSERDU at current dose level.
Grade 2 | Consider interruption of ORSERDU until recovery to Grade ≤ 1 or baseline. Then resume ORSERDU at the same dose level.
Grade 3 | Interrupt ORSERDU until recovery to Grade ≤ 1 or baseline. Then resume ORSERDU at the next lower dose level. If the Grade 3 toxicity recurs, interrupt ORSERDU until recovery to Grade ≤ 1 or baseline. Then resume ORSERDU reduced by another dose level.
Grade 4 | Interrupt ORSERDU until recovery to Grade ≤ 1 or baseline. Then resume ORSERDU reduced by one dose level. If a Grade 4 or intolerable adverse reaction recurs, permanently discontinue ORSERDU.

2.4 Dosage Modifications for Use with Concomitant CYP3A4 Inducers and Inhibitors

Avoid concomitant use of ORSERDU with strong or moderate CYP3A4 inducers and inhibitors [see Drug Interactions (7.1)].

2.5 Dosage Modifications for Hepatic Impairment

Avoid use of ORSERDU in patients with severe hepatic impairment (Child-Pugh C). Reduce the ORSERDU dosage to 258 mg once daily for patients with moderate hepatic impairment (Child-Pugh B). No dosage adjustment is recommended for patients with mild hepatic impairment (Child-Pugh A) [see Clinical Pharmacology (12.3)].

3 DOSAGE FORMS AND STRENGTHS

Tablets: Elacestrant 345 mg (equivalent to 400 mg elacestrant hydrochloride) and 86 mg (equivalent to 100 mg elacestrant hydrochloride):

- 345 mg: light blue, unscored, oval film-coated biconvex tablet, imprinted with “MH” on one side and plain on the other side.
- 86 mg: light blue, unscored, round film-coated biconvex tablet, imprinted with “ME” on one side and plain on the other side.

4 CONTRAINDICATIONS

None.

5 WARNINGS AND PRECAUTIONS

5.1 Dyslipidemia

Hypercholesterolemia and hypertriglyceridemia occurred in patients taking ORSERDU at an incidence of 30% and 27%, respectively. The incidence of Grade 3 and 4 hypercholesterolemia and hypertriglyceridemia were 0.9% and 2.2%, respectively [see Adverse Reactions (6.1)].

Monitor lipid profile prior to starting and periodically while taking ORSERDU.

5.2 Embryo-Fetal Toxicity

Based on findings in animals and its mechanism of action, ORSERDU can cause fetal harm when administered to a pregnant woman. Administration of elacestrant to pregnant rats resulted in adverse developmental outcomes, including embryo-fetal mortality and structural abnormalities, at maternal exposures below the recommended dose based on area under the curve (AUC).

Advise pregnant women and females of reproductive potential of the potential risk to a fetus. Advise females of reproductive potential to use effective contraception during treatment with ORSERDU and for 1 week after the last dose. Advise male patients with female partners of reproductive potential to use effective contraception during treatment with ORSERDU and for 1 week after the last dose [see Use in Specific Populations (8.1, 8.3) and Clinical Pharmacology (12.1)].

6 ADVERSE REACTIONS

The following clinically significant adverse reactions are described elsewhere in the labeling:

- Dyslipidemia [see Warnings and Precautions (5.1)]

6.1 Clinical Trials Experience

Because clinical trials are conducted under widely varying conditions, adverse reaction rates observed in the clinical trials of a drug cannot be directly compared to rates in the clinical trials of another drug and may not reflect the rates observed in practice.

The safety of ORSERDU was evaluated in 467 patients with ER+/HER2- advanced breast cancer following CDK4/6 inhibitor therapy in EMERALD, a randomized, open-label, multicenter study [see Clinical Studies (14)]. Patients received ORSERDU 345 mg orally once daily (n=237) or standard of care (SOC) consisting of fulvestrant or an aromatase inhibitor (n=230). Among patients who received ORSERDU, 22% were exposed for 6 months or longer and 9% were exposed for greater than one year.

Serious adverse reactions occurred in 12% of patients who received ORSERDU. Serious adverse reactions in >1% of patients who received ORSERDU were musculoskeletal pain (1.7%) and nausea (1.3%). Fatal adverse reactions occurred in 1.7% of patients who received ORSERDU, including cardiac arrest, septic shock, diverticulitis, and unknown cause (one patient each).

Permanent discontinuation of ORSERDU due to an adverse reaction occurred in 6% of patients. Adverse reactions which resulted in permanent discontinuation of ORSERDU in >1% of patients were musculoskeletal pain (1.7%) and nausea (1.3%).

Dosage interruptions of ORSERDU due to an adverse reaction occurred in 15% of patients. Adverse reactions which resulted in dosage interruption of ORSERDU in >1% of patients were nausea (3.4%), musculoskeletal pain (1.7%), and increased ALT (1.3%).

Dosage reductions of ORSERDU due to an adverse reaction occurred in 3% of patients. Adverse reactions which required dosage reductions of ORSERDU in >1% of patients were nausea (1.7%).

The most common (≥10%) adverse reactions, including laboratory abnormalities, of ORSERDU were musculoskeletal pain, nausea, increased cholesterol, increased AST, increased triglycerides, fatigue, decreased hemoglobin, vomiting, increased ALT, decreased sodium, increased creatinine, decreased appetite, diarrhea, headache, constipation, abdominal pain, hot flush, and dyspepsia.

Table 3 summarizes the adverse reactions in EMERALD.

Table 3: Adverse Reactions (>10%) in Patients with ER-positive, HER2-negative, Advanced or Metastatic Breast Cancer Who Received ORSERDU in EMERALDa

Adverse Reaction | ORSERDU (n=237) |  | Fulvestrant or an Aromatase Inhibitor (n=230)
Adverse Reaction | All Grades (%) | Grade 3 or 4 c (%) | All Grades (%) | Grade 3 or 4 c (%)
Musculoskeletal and connective tissue disorders
Musculoskeletal painb | 41 | 7 | 39 | 1
Gastrointestinal disorders
Nausea | 35 | 2.5 | 19 | 0.9
Vomitingb | 19 | 0.8 | 9 | 0
Diarrhea | 13 | 0 | 10 | 1
Constipation | 12 | 0 | 6 | 0
Abdominal painb | 11 | 1 | 10 | 0.9
Dyspepsia | 10 | 0 | 2.6 | 0
General disorders
Fatigueb | 26 | 2 | 27 | 1
Metabolism and nutrition disorders
Decreased appetite | 15 | 0.8 | 10 | 0.4
Nervous system
Headache | 12 | 2 | 12 | 0
Vascular disorders
Hot flush | 11 | 0 | 8 | 0
aAdverse reactions were graded using NCI CTCAE version 5.0.
bIncludes other related terms
cOnly includes Grade 3 adverse reactions.

Clinically relevant adverse reactions in < 10% of patients who received ORSERDU included rash, insomnia, dyspnea, cough, dizziness, stomatitis and gastroesophageal reflux disease.

Table 4 summarizes the laboratory abnormalities in EMERALD.

Table 4: Select Laboratory Abnormalities (>10%) That Worsened from Baseline in Patients with ER-positive, HER2-negative, Advanced or Metastatic Breast Cancer Who Received ORSERDU in EMERALDa

Laboratory Abnormality | ORSERDUa |  | Fulvestrant or an Aromatase Inhibitora
Laboratory Abnormality | All Grades (%) | Grade 3 or 4 (%) | All Grades (%) | Grade 3 or 4 (%)
Chemistry
Cholesterol increased | 30 | 1 | 17 | 0
Aspartate aminotransferase increased | 29 | 0 | 34 | 1
Triglycerides increased | 27 | 2 | 15 | 1
Alanine aminotransferase increased | 17 | 0 | 24 | 1
Sodium decreased | 16 | 1 | 15 | 0
Creatinine increased | 16 | 0 | 6 | 0
Hematology
Hemoglobin decreased | 26 | 1 | 20 | 2
aThe denominator used to calculate the rate varied from 29 to 236 for ORSERDU and from 37 to 225 for fulvestrant or an aromatase inhibitor based on the number of patients with a baseline value and at least one post-treatment value.

7 DRUG INTERACTIONS

7.1 Effect of Other Drugs on ORSERDU

Strong and Moderate CYP3A4 Inhibitors

Avoid concomitant use of strong or moderate CYP3A inhibitors with ORSERDU.

Elacestrant is a CYP3A4 substrate. Concomitant use of a strong or moderate CYP3A4 inhibitor increase elacestrant exposure [see Clinical Pharmacology (12.3)], which may increase the risk of adverse reactions of ORSERDU.

Strong and Moderate CYP3A4 Inducers

Avoid concomitant use of strong or moderate CYP3A inducers with ORSERDU.

Elacestrant is a CYP3A4 substrate. Concomitant use of a strong or moderate CYP3A4 inducer decreases elacestrant exposure [see Clinical Pharmacology (12.3)], which may decrease effectiveness of ORSERDU.

7.2 Effect of ORSERDU on Other Drugs

P-gp Substrates

Reduce the dosage of P-gp substrates per their Prescribing Information when minimal concentration changes may lead to serious or life-threatening adverse reactions.

Elacestrant is a P-gp inhibitor. Concomitant use of ORSERDU with a P-gp substrate increased the concentrations of P-gp substrate [see Clinical Pharmacology (12.3)], which may increase the adverse reactions associated with a P-gp substrate.

BCRP Substrates

Reduce the dosage of BCRP substrates per their Prescribing Information when minimal concentration changes may lead to serious or life-threatening adverse reactions.

Elacestrant is a BCRP inhibitor. Concomitant use of ORSERDU with a BCRP substrate increased the plasma concentrations of BCRP substrate [see Clinical Pharmacology (12.3)], which may increase the adverse reactions associated with a BCRP substrate.

8 USE IN SPECIFIC POPULATIONS

8.1 Pregnancy

Risk Summary

Based on findings in animals and its mechanism of action, ORSERDU can cause fetal harm when administered to a pregnant woman [see Clinical Pharmacology (12.1)]. There are no available human data on ORSERDU use in pregnant women to inform the drug-associated risk. In an animal reproduction study, oral administration of elacestrant to pregnant rats during organogenesis caused embryo-fetal mortality and structural abnormalities at maternal exposures below the recommended dose based on AUC (see Data). Advise pregnant women and females of reproductive potential of the potential risk to a fetus.

The background risk of major birth defects and miscarriage for the indicated population is unknown. In the U.S. general population, the estimated background risk of major birth defects and miscarriage in clinically recognized pregnancies is 2%-4% and 15%-20%, respectively.

Data

Animal Data

In an embryo-fetal development study in pregnant rats, administration of oral doses of elacestrant up to 30 mg/kg/day during the period of organogenesis resulted in maternal toxicity (reduced body weight gain, low food consumption, red vulvar discharge) and embryo-fetal mortality (increased resorptions, post-implantation loss, and reduced number of live fetuses) at ≥ 3 mg/kg/day (approximately 0.1 times the human AUC at the recommended dose). Additional adverse effects included reduced fetal weight and external malformations of the limbs (hyperflexion, malrotation) and head (domed, misshapen, flattened) with corresponding skeletal malformations of the skull at doses ≥ 10 mg/kg/day (approximately 0.5 times the human AUC at the recommended dose).

8.2 Lactation

Risk Summary

There are no data on the presence of elacestrant in human milk, its effects on milk production, or the breastfed child. Because of the potential for serious adverse reactions in the breastfed child, advise lactating women to not breastfeed during treatment with ORSERDU and for 1 week after the last dose.

8.3 Females and Males of Reproductive Potential

ORSERDU can cause fetal harm when administered to a pregnant woman [see Use in Specific Populations (8.1)].

Pregnancy Testing

Verify the pregnancy status in females of reproductive potential prior to initiating ORSERDU treatment.

Contraception

Females

Advise females of reproductive potential to use effective contraception during treatment with ORSERDU and for 1 week after the last dose.

Males

Advise male patients with female partners of reproductive potential to use effective contraception during treatment with ORSERDU and for 1 week after the last dose.

Infertility

Based on findings from animal studies, ORSERDU may impair fertility in females and males of reproductive potential [see Nonclinical Toxicology (13.1)].

8.4 Pediatric Use

The safety and effectiveness of ORSERDU in pediatric patients have not been established.

8.5 Geriatric Use

Of 237 patients who received ORSERDU in the EMERALD trial, 43% were 65 years of age or older and 17% were 75 years of age or older. No overall differences in safety or effectiveness of ORSERDU were observed between patients 65 years or older of age compared to younger patients. There are an insufficient number of patients 75 years of age or older to assess whether there are differences in safety or effectiveness.

8.6 Hepatic Impairment

Avoid use of ORSERDU in patients with severe hepatic impairment (Child-Pugh C). Reduce the dose of ORSERDU in patients with moderate hepatic impairment (Child-Pugh B). No dosage adjustment is recommended for patients with mild hepatic impairment (Child-Pugh A) [see Dosage and Administration (2.5) and Clinical Pharmacology (12.3)].

11 DESCRIPTION

Elacestrant hydrochloride is the salt form of elacestrant, an estrogen receptor antagonist, that has the chemical name: (6R)-6-(2-(N-(4-(2-(ethylamino)ethyl)benzyl)-N-ethylamino)-4-methoxyphenyl)-5,6,7,8-tetrahydronaphthalen-2-ol dihydrochloride. Elacestrant hydrochloride is the dihydrochloride salt and the molecular formula is C30H38N2O2.2HCL. The relative molecular mass is 531.56 g/mol. The chemical structure of elacestrant hydrochloride is shown below:

Elacestrant hydrochloride is a white to off-white to grey solid and is freely soluble in 0.01N HCI.

ORSERDU (elacestrant) 345 mg film-coated tablet contains 400 mg of elacestrant hydrochloride (approximately 345 mg of elacestrant free base).

ORSERDU (elacestrant) 86 mg film-coated tablet contains 100 mg of elacestrant hydrochloride (approximately 86 mg of elacestrant free base).

Both tablet strengths contain the following inactive ingredients: colloidal silicon dioxide, crospovidone, magnesium stearate (non-bovine), microcrystalline cellulose, and silicified microcrystalline cellulose. The tablets also contain Opadry II Blue (polyvinyl alcohol, titanium dioxide, polyethylene glycol, FD&C Blue #1 and talc).

12 CLINICAL PHARMACOLOGY

12.1 Mechanism of Action

Elacestrant is an estrogen receptor antagonist that binds to estrogen receptor-alpha (ERα). In ER-positive (ER+) HER2-negative (HER2-) breast cancer cells, elacestrant inhibited 17β-estradiol mediated cell proliferation at concentrations inducing degradation of ERα protein mediated through proteasomal pathway. Elacestrant demonstrated in vitro and in vivo antitumor activity including in ER+ HER2- breast cancer models resistant to fulvestrant and cyclin-dependent kinase 4/6 inhibitors and those harboring estrogen receptor 1 gene (ESR1) mutations.

12.2 Pharmacodynamics

Elacestrant exposure-response relationships and the time course of pharmacodynamics have not been fully characterized.

Cardiac Electrophysiology

ORSERDU does not cause a mean increase in QTc interval > 20 msec at the approved recommended dose.

12.3 Pharmacokinetics

The steady-state mean (%CV) maximum concentration (Cmax) of elacestrant is 119 ng/mL (43.6%) and the area under the concentration-time curve (AUC0-24h) is 2440 ng*h/mL (44.3%) after administration of the recommended dosage of 345 mg once daily. The Cmax and AUC of elacestrant increase more than proportionally over a dosage range from 43 mg to 862 mg once daily (0.125 to 2.5 times the approved recommended dosage). Steady state is reached by Day 6 and the mean accumulation ratio based on AUC0-24h is 2-fold.

Absorption

The time to achieve peak plasma concentration (tmax) ranges from 1 to 4 hours. The elacestrant oral bioavailability is approximately 10%.

Effect of Food

Administration of ORSERDU 345 mg with a high-fat meal (800 to 1000 calories, 50% fat) increased Cmax by 42% and AUC by 22% compared to fasted administration.

Distribution

The estimated apparent volume of distribution is 5800L. Plasma protein binding of elacestrant is >99% and independent of concentration.

Elimination

The elimination half-life of elacestrant is 30 to 50 hours. The estimated mean (% CV) clearance of elacestrant is 186 L/hr (43.5%) and renal clearance is ≤ 0.14 L/hr.

Metabolism

Elacestrant is primarily metabolized by CYP3A4 and to a lesser extent by CYP2A6 and CYP2C9.

Excretion

Following a single radiolabeled oral dose of 345 mg, 82% was recovered in feces (34% unchanged) and 7.5% was recovered in urine (< 1% unchanged).

Specific Populations

There were no clinically significant differences in the pharmacokinetics of elacestrant based on age (24 to 89 years), sex, and body weight (41 to 143 kg).

Patients with Hepatic Impairment

There were no clinically significant differences in the Cmax and AUC of elacestrant in subjects with mild hepatic impairment (Child-Pugh A). The AUC of elacestrant increased in subjects with moderate hepatic impairment (Child-Pugh B) by 83%.

Elacestrant has not been studied in subjects with severe hepatic impairment (Child-Pugh C).

Drug Interaction Studies

Clinical Studies

There were no clinically significant differences in the pharmacokinetics of elacestrant when used concomitantly with cimetidine (weak CYP3A inhibitor), omeprazole (gastric acid-reducing agent), or warfarin (highly protein-bound drug).

Table 5 describes the effect of other drugs on the pharmacokinetics of elacestrant and Table 6 describes the effect of elacestrant on the pharmacokinetics of other drugs.

Table 5: Effect of Other Drugs on Elacestrant

Concomitant Drug | Elacestrant Dose | Fold Increased or Percent Decrease of Elacestrant With Concomitant Drug
Concomitant Drug | Elacestrant Dose | Cmax | AUC
CYP3A Inhibitors
Strong Inhibitor Itraconazole | 172 mg once daily | 4.4 | 5.3
Moderate Inhibitor Fluconazolea | 345 mg single dose | 1.6 | 2.3
CYP3A Inducers
Strong Inducer Rifampin | 345 mg single dose | 73% | 86%
Moderate Inducer Efavirenza | 345 mg single dose | 44-63% | 55-73%
aPredicted changes in Cmax and AUC of elacestrant.

Table 6: Effect of Elacestrant on Other Drugs

Concomitant Drug | Elacestrant Dose | Fold Increase of Concomitant Drug With Elacestrant
Concomitant Drug | Elacestrant Dose | Cmax | AUC
Substrate of P-gp
Digoxin | 345 mg single dose | 1.3 | 1.1
Substrate of BCRP
Rosuvastatin | 345 mg single dose | 1.5 | 1.2

In Vitro Studies

Cytochrome P450 (CYP) Enzymes: Elacestrant is not an inhibitor of CYP1A2, CYP2A6, CYP2B6, CYP2C8, CYP2C9, CYP2C19, CYP2D6, CYP2E1, or CYP3A.

Elacestrant is not an inducer of CYP1A2, CYP2A6, CYP2B6, CYP2C9, CYP2C19, or CYP3A.

Transporter Systems: Elacestrant is a substrate for OATP2B1, but not P-gp.

Elacestrant is not an inhibitor of OAT1, OAT3, OCT2, MATE1, MATE2-K, OCT1, OATP1B1, OATP1B3 or OATP2B1.

13 NONCLINICAL TOXICOLOGY

13.1 Carcinogenesis, Mutagenesis, Impairment of Fertility

Carcinogenicity studies have not been conducted with elacestrant.

Elacestrant was not mutagenic in an in vitro bacterial reverse mutation (Ames) assay or clastogenic in either in vitro chromosome aberration assays or an in vivo rat bone marrow micronucleus assay.

Fertility studies with elacestrant in animals have not been conducted. In repeated-dose toxicity studies up to 26 weeks duration in rats and 39 weeks duration in cynomolgus monkeys, adverse reactions were observed in female reproductive organs including atrophy of the vagina, cervix, and uterus and follicular cysts in the ovary at doses ≥ 10 mg/kg/day in rats and cynomolgus monkeys (≥ 0.3 times the human AUC at the recommended dose). Decreased cellularity of Leydig cells and degeneration/atrophy of the seminiferous epithelium in the testis were observed in male rats at a dose of 50 mg/kg/day (approximately 2.6 times the human AUC at the recommended dose).

14 CLINICAL STUDIES

The efficacy of ORSERDU was evaluated in EMERALD (NCT03778931), a randomized, open-label, active-controlled, multicenter trial that enrolled 478 postmenopausal women and men with ER+/HER2- advanced or metastatic breast cancer of which 228 patients had ESR1 mutations. Patients were required to have disease progression on one or two prior lines of endocrine therapy, including one line containing a CDK4/6 inhibitor. Eligible patients could have received up to one prior line of chemotherapy in the advanced or metastatic setting.

Patients were randomized (1:1) to receive ORSERDU 345 mg orally once daily (n=239), or investigator’s choice of endocrine therapy (n=239), which included fulvestrant (n=166), or an aromatase inhibitor (n=73; anastrozole, letrozole or exemestane). Randomization was stratified by ESR1 mutation status (detected vs not detected), prior treatment with fulvestrant (yes vs no), and visceral metastasis (yes vs no). ESR1 mutational status was determined by blood circulating tumor deoxyribonucleic acid (ctDNA) using the Guardant360 CDx assay and was limited to ESR1 missense mutations in the ligand binding domain (between codons 310 to 547). Patients were treated until disease progression or unacceptable toxicity.

The major efficacy outcome was progression-free survival (PFS), assessed by a blinded imaging review committee (BIRC). An additional efficacy outcome measure was overall survival (OS).

A statistically significant difference in PFS was observed in the intention to treat (ITT) population and in the subgroup of patients with ESR1 mutations. An exploratory analysis of PFS in the 250 (52%) patients without ESR1 mutations showed a HR 0.86 (95% CI: 0.63, 1.19) indicating that the improvement in the ITT population was primarily attributed to the results seen in the ESR1 mutated population.

Among the patients with ESR1 mutations (n=228), the median age was 63 years (range: 28-89); 100% were female; 72% were White, 5.7% Asian, 3.5% Black, 0.4% Other, 18.4% unknown/not reported; 8.8% were Hispanic/Latino; and baseline ECOG performance status was 0 (57%) or 1 (43%). Most patients had visceral disease (71%); 62% had received 1 line of endocrine therapy and 39% had received 2 lines of endocrine therapy in the advanced or metastatic setting. All patients had received prior treatment with a CDK4/6 inhibitor, 24% had received prior fulvestrant, and 25% had received prior chemotherapy in the advanced or metastatic setting.

Efficacy results are presented in Table 7 and Figure 1 for patients with ESR1 mutations.

Table 7: Efficacy Results for EMERALD (Patients with ESR1 Mutations)

 | ORSERDU (N = 115) | Fulvestrant or an Aromatase Inhibitor (N=113)
Progression-free Survival (PFS)a
Number of PFS Events, n (%) | 62 (54) | 78 (69)
Median PFS monthsb (95% CI) | 3.8 (2.2, 7.3) | 1.9 (1.9, 2.1)
Hazard ratioc (95% CI) | 0.55 (0.39, 0.77)
p-valued | 0.0005
Overall Survival (OS)
Number of OS Events, n (%) | 61 (53) | 60 (53)
Hazard ratioc (95% CI) | 0.90 (0.63, 1.30)
p-valued | NSe
CI=confidence interval; ESR1=estrogen receptor 1
aPFS results based on blinded imaging review committee.
bKaplan-Meier estimate; 95% CI based on the Brookmeyer-Crowley method using a linear transformation.
cCox proportional hazards model stratified by prior treatment with fulvestrant (yes vs no) and visceral metastasis (yes vs no).
dStratified log-rank test two-sided p-value.
eNS – Not statistically significant.

Figure 1: Kaplan-Meier Curve for PFS in EMERALD (Patients with ESR1 Mutations, BIRC Assessment)

^+ Censored times

16 HOW SUPPLIED/STORAGE AND HANDLING

ORSERDU (elacestrant) film-coated tablets for oral use are supplied as follows:

Tablet Strength | Tablet Color and Shape | Tablet Markings | Pack Size | NDC Code
Elacestrant 345 mg (equivalent to 400 mg elacestrant hydrochloride) | Light blue; Oval | “MH” | Bottle of 30 Tablets with Child Resistant Closure (CRC). | NDC 72187-0102-3
Elacestrant 86 mg (equivalent to 100 mg elacestrant hydrochloride) | Light blue; Round | “ME” | Bottle of 30 Tablets with Child Resistant Closure (CRC). | NDC 72187-0101-3

Storage and Handling

Store at 20°C to 25°C (68°F to 77°F). Excursions permitted from 15°C to 30°C (59°F to 86°F). [see USP controlled room temperature].

17 PATIENT COUNSELING INFORMATION

Advise the patient to read the FDA-approved patient labeling (Patient Information).

Dyslipidemia

Advise patients that hypercholesterolemia and hypertriglyceridemia may occur while taking ORSERDU. Inform patients that lipid profile monitoring will be performed prior to starting and periodically while taking ORSERDU [see Warnings and Precautions (5.1) and Adverse Reactions (6.1)].

Embryo-Fetal Toxicity

Advise pregnant women and females of reproductive potential of the potential risk to a fetus. Advise females to inform their healthcare provider of a known or suspected pregnancy [see Warnings and Precautions (5.2) and Use in Specific Populations (8.1)].

Advise females of reproductive potential to use effective contraception during treatment with ORSERDU and for 1 week after the last dose. Advise male patients with female partners of reproductive potential to use effective contraception during treatment with ORSERDU and for 1 week after the last dose [see Use in Specific Populations (8.3)].

Lactation

Advise women not to breastfeed during treatment with ORSERDU and for 1 week after the last dose [see Use in Specific Populations (8.2)].

Infertility

Advise males and females of reproductive potential that ORSERDU may impair fertility [see Use in Specific Populations (8.3)].

Drug Interactions

Advise patients to inform their healthcare providers of all concomitant medications, including prescription medicines, over-the-counter drugs, and herbal products [see Drug Interactions (7.1, 7.2)].

Other Common Adverse Reactions

Advise patients that other adverse reactions with ORSERDU treatment may include musculoskeletal pain, nausea, fatigue, vomiting, decreased appetite, diarrhea, headache, constipation, abdominal pain, hot flush, and dyspepsia, [see Adverse Reactions (6.1)].

Dosing Instructions

Instruct patients to take ORSERDU at approximately the same time each day and to swallow the tablet(s) whole. Tablets should not be chewed, crushed, or split prior to swallowing [see Dosage and Administration (2.2)].

Advise patients to take ORSERDU with food to reduce nausea and vomiting [see Dosage and Administration (2.2) and Adverse Reactions (6.1)].

Instruct patients that if a dose of ORSERDU is missed for more than 6 hours or vomiting occurs, skip the dose and take the next dose the following day at its regularly scheduled time [see Dosage and Administration (2.2)].

ORSERDU is a trademark of the Menarini Group.
©Stemline Therapeutics, Inc., a Menarini Group company
Manufactured for: Stemline Therapeutics, Inc., New York, NY 10022

PATIENT INFORMATION

ORSERDU™ (or-SER-doo)
(elacestrant)
tablets

What is ORSERDU?

ORSERDU is a prescription medicine to treat women who have gone through menopause and adult men with estrogen receptor (ER)-positive, human epidermal growth factor receptor 2 (HER2)-negative, ESR1-mutated advanced breast cancer or breast cancer that has spread to other parts of the body (metastatic), and whose disease has progressed after endocrine therapy.

Your healthcare provider will perform a test to make sure that ORSERDU is right for you.

It is not known if ORSERDU is safe and effective in children.

Before taking ORSERDU, tell your healthcare provider about all of your medical conditions, including if you:

- have liver problems
- are pregnant or plan to become pregnant. ORSERDU can harm your unborn baby.
  Females who are able to become pregnant:
  - Your healthcare provider may do a pregnancy test before you start treatment with ORSERDU.
  - You should use effective (contraception) birth control during treatment with ORSERDU and for 1 week after the last dose.
  - Tell your healthcare provider right away if you become pregnant or think you may be pregnant during treatment with ORSERDU.
  Males with female partners who are able to become pregnant:
  - You should use effective (contraception) birth control during treatment with ORSERDU and for 1 week after the last dose.

- are breastfeeding or plan to breastfeed. It is not known if ORSERDU passes into your breast milk. Do not breastfeed during treatment with ORSERDU and for 1 week after the last dose.

Tell your healthcare provider about all of the medicines you take, including prescription and over-the counter medicines, vitamins, and herbal supplements. ORSERDU and other medicines may affect each other causing side effects. Know the medicines you take. Keep a list of them to show your healthcare provider or pharmacist when you get a new medicine.

How should I take ORSERDU?

- Take ORSERDU exactly as your healthcare provider tells you.
- Do not change your dose or stop taking ORSERDU unless your healthcare provider tells you.
- Take ORSERDU 1 time each day, at about the same time each day.
- Take ORSERDU with food. Taking ORSERDU with food may help reduce nausea and vomiting.
- Swallow ORSERDU tablets whole. Do not chew, crush or split the tablets before swallowing.
- Do not take any ORSERDU tablets that are broken, cracked, or that look damaged.
- If you miss a dose of ORSERDU or vomit after taking a dose of ORSERDU, do not take another dose of ORSERDU on that day. Skip the dose and take your next dose the following day at your regularly scheduled time.

What are the possible side effects of ORSERDU?

ORSERDU may cause serious side effects, including:

- Increased fat (lipid) levels in your blood (hypercholesterolemia and hypertriglyceridemia). Your healthcare provider will do blood tests to check your lipid levels before and during your treatment with ORSERDU.

The most common side effects of ORSERDU include:

- muscle and joint (musculoskeletal) pain
- nausea
- increased cholesterol and triglyceride levels in your blood
- increased liver function tests
- tiredness
- decreased red blood cell counts
- vomiting
- decreased salt (sodium) levels in your blood
- increased kidney function test
- decreased appetite
- diarrhea
- headache
- constipation
- stomach-area (abdominal) pain
- hot flush
- indigestion or heartburn

Your healthcare provider may decrease your dose, temporarily stop, or completely stop treatment with ODSERDU, if you develop certain side effects.

ORSERDU may affect fertility in males and in females who are able to become pregnant. Talk to your healthcare provider if this is a concern for you.

These are not all of the possible side effects of ORSERDU.

Call your doctor for medical advice about side effects. You may report side effects to FDA at 1-800-FDA-1088.

How should I store ORSERDU?

- Store ORSERDU at room temperature 68℉ to 77℉ (20℃ to 25℃).

Keep ORSERDU and all medicines out of the reach of children.

General information about the safe and effective use of ORSERDU.

Medicines are sometimes prescribed for purposes other than those listed in a Patient Information leaflet. Do not use ORSERDU for a condition for which it was not prescribed. Do not give ORSERDU to other people, even if they have the same symptoms you have. It may harm them. You can ask your healthcare provider or pharmacist for more information about ORSERDU that is written for health professionals.

What are the ingredients in ORSERDU?

Active ingredient: elacestrant

Inactive ingredients: colloidal silicon dioxide, crospovidone, magnesium stearate (non-bovine), microcrystalline cellulose, silicified microcrystalline cellulose and Opadry II Blue (polyvinyl alcohol, titanium dioxide, polyethylene glycol, FD&C Blue #1 and talc).

ORSERDU is a trademark of the Menarini Group.

©Stemline Therapeutics, Inc., a Menarini Group Company

Manufactured for: Stemline Therapeutics, Inc., New York, NY 10022

For more information, go to www.ORSERDU.com or call 1-877-332-7961

This Patient Information has been approved by the U.S. Food and Drug Administration.

Issued: 01/2023

PRINCIPAL DISPLAY PANEL - NDC:72187-0101-3 - Orserdu Bottle Label - 86mg

NDC 72187-0101-3

Orserdu®
(elacestrant) tablets

86 mg

Rx Only

30 Tablets

PRINCIPAL DISPLAY PANEL - NDC: 72187-0102-3 - Orserdu Bottle Label - 345mg

NDC 72187-0102-3

Orserdu®
(elacestrant) tablets

345 mg

Rx Only

30 Tablets